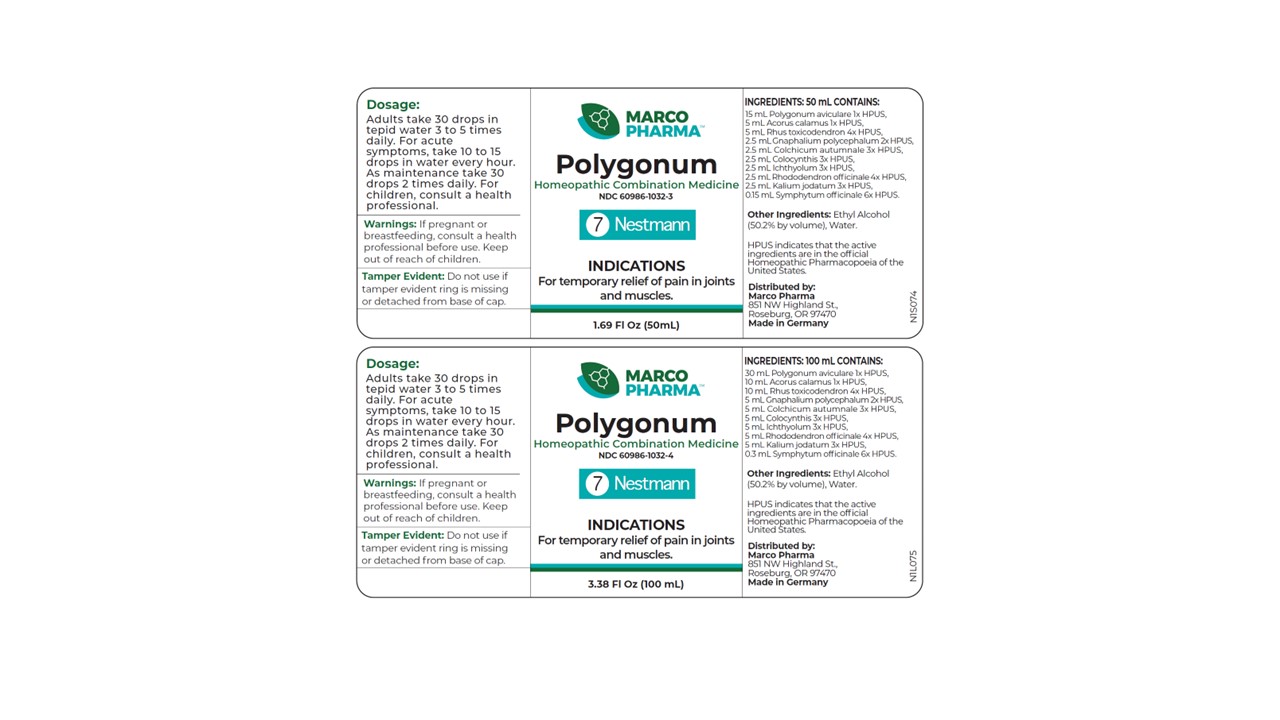 DRUG LABEL: Polygonum
NDC: 60986-1032 | Form: LIQUID
Manufacturer: Marco Pharma International LLC.
Category: homeopathic | Type: HUMAN OTC DRUG LABEL
Date: 20260112

ACTIVE INGREDIENTS: POLYGONUM AVICULARE TOP 1 [hp_X]/100 mL; CITRULLUS COLOCYNTHIS FRUIT PULP 3 [hp_X]/100 mL; COMFREY ROOT 6 [hp_X]/100 mL; COLCHICUM AUTUMNALE BULB 3 [hp_X]/100 mL; POTASSIUM IODIDE 4 [hp_X]/100 mL; RHODODENDRON AUREUM LEAF 3 [hp_X]/100 mL; TOXICODENDRON PUBESCENS LEAF 4 [hp_X]/100 mL; PSEUDOGNAPHALIUM OBTUSIFOLIUM 2 [hp_X]/100 mL; ACORUS CALAMUS WHOLE 1 [hp_X]/100 mL; ICHTHAMMOL 3 [hp_X]/100 mL
INACTIVE INGREDIENTS: WATER; ALCOHOL

Drug Facts

ACTIVE INGREDIENT

Buckwheat 1x HPUS

Sweetflag 1x HPUS

Poison oak 4x HPUS

Common everlasting 2x HPUS

Golden flower rhododendron 3x HPUS

Colocynth 3x HPUS

Meadow saffron 3x HPUS

Potassium iodide 4x HPUS

Ichthammol 3x HPUS

Comfrey 6x HPUS

HPUS indicates that the active ingredients in this product are in the official Homeopathic Pharmacopoeia of the United States.

DOSAGE AND ADMINISTRATION

Adults take 30 drops in tepid water three to five times daily.

For acute symptoms, take 10-15 drops in water every hour.

As maintenance, take 30 drops two times daily.

For children, please discuss with a health professional.

WARNINGS

If pregnant or breast-feeding, consult a health professional before use.

Keep out of the reach of children.

INACTIVE INGREDIENT

Other ingredients: Ethyl Alcohol (50.2% by vol.) and Water.

INDICATIONS AND USAGE

Indications: For temporary relief of pain in joints and muscles.

PURPOSE

For relief of pain in joints and muscles.